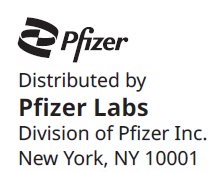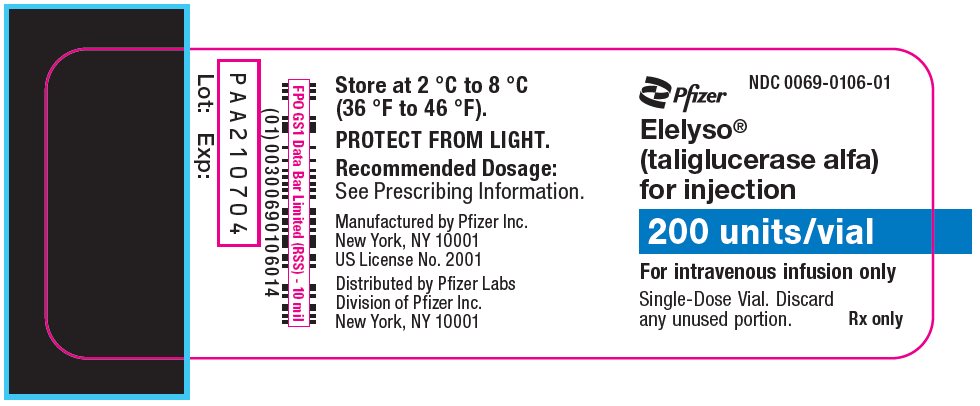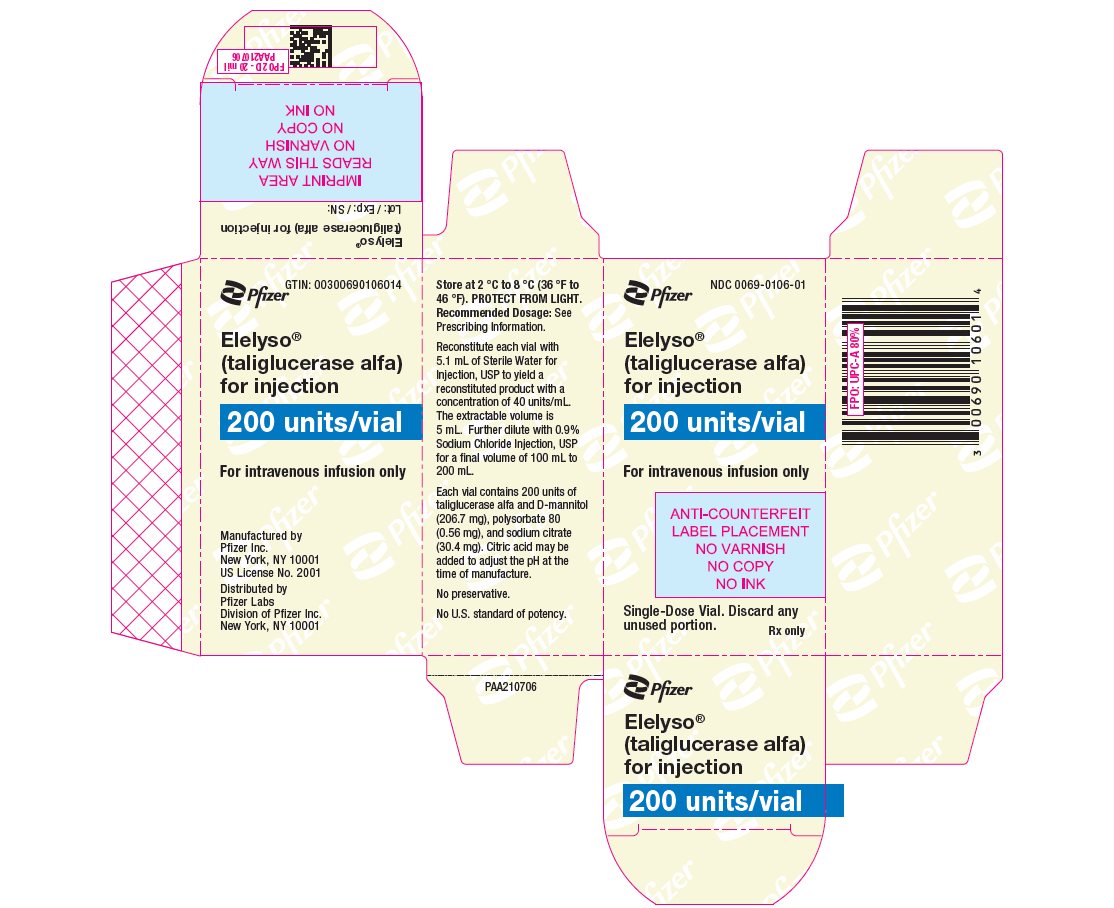 DRUG LABEL: ELELYSO
NDC: 0069-0106 | Form: INJECTION, POWDER, LYOPHILIZED, FOR SOLUTION
Manufacturer: Pfizer Laboratories Div Pfizer Inc
Category: prescription | Type: HUMAN PRESCRIPTION DRUG LABEL
Date: 20251229

ACTIVE INGREDIENTS: TALIGLUCERASE ALFA 200 U/5 mL
INACTIVE INGREDIENTS: MANNITOL 206.7 mg/5 mL; POLYSORBATE 80 0.56 mg/5 mL; SODIUM CITRATE, UNSPECIFIED FORM 30.4 mg/5 mL

HIGHLIGHTS OF PRESCRIBING INFORMATION

These highlights do not include all the information needed to use ELELYSO safely and effectively. See full prescribing information for ELELYSO.
ELELYSO® (taliglucerase alfa) for injection, for intravenous use
Initial U.S. Approval: 2012

RECENT MAJOR CHANGES

Warnings and Precautions (5.1) | 1/2025

WARNING: HYPERSENSITIVITY REACTIONS INCLUDING ANAPHYLAXIS

See full prescribing information for complete boxed warning.

- Anaphylaxis has occurred during the early course of enzyme replacement therapy and after extended duration of therapy. (5.1)
- Initiate ELELYSO in a healthcare setting with appropriate medical monitoring and support measures, including access to cardiopulmonary resuscitation equipment. (5.1)
- If a severe hypersensitivity reaction (e.g., anaphylaxis) occurs, discontinue ELELYSO and immediately initiate appropriate medical treatment, including use of epinephrine. (5.1)

1 INDICATIONS AND USAGE

ELELYSO is a hydrolytic lysosomal glucocerebroside-specific enzyme indicated for the treatment of patients 4 years and older with a confirmed diagnosis of Type 1 Gaucher disease (1).

2 DOSAGE AND ADMINISTRATION

Recommendations Prior to ELELYSO Treatment (2.1):

- Administration of ELELYSO should be supervised by a healthcare provider knowledgeable in the management of hypersensitivity reactions including anaphylaxis.

Recommended Dosage in Patients 4 Years and Older (2.2):

- Treatment-naïve: 60 units/kg administered every other week as a 60- to 120-minute intravenous infusion.
- Patients switching from imiglucerase: Initiate ELELYSO intravenous treatment (60- to 120-minute infusion) with the same units/kg imiglucerase dosage and subsequently administer ELELYSO every other week. Dosage adjustments can be based on achievement and maintenance of each patient’s therapeutic goals.

Preparation and Administration (2.3, 2.4, 2.5):

- Reconstitute, dilute and administer under the supervision of a healthcare professional.
- See Full Prescribing Information for complete instructions.

3 DOSAGE FORMS AND STRENGTHS

For injection: 200 units lyophilized powder in a single-dose vial for reconstitution (3)

4 CONTRAINDICATIONS

None (4)

5 WARNINGS AND PRECAUTIONS

See boxed warning (5.1)

6 ADVERSE REACTIONS

The most common adverse reactions are:

- Treatment-Naïve Adults (≥5%): headache, arthralgia, fatigue, nausea, dizziness, abdominal pain, pruritus, flushing, vomiting, urticaria (6.1).
- Patients who Switched from Imiglucerase, after 9 Months on Treatment (≥10%): arthralgia, headache, pain in extremity (6.1).

To report SUSPECTED ADVERSE REACTIONS, contact Pfizer Inc. at 1-800-438-1985 or FDA at 1-800-FDA-1088 or www.fda.gov/medwatch.

FULL PRESCRIBING INFORMATION

WARNING: HYPERSENSITIVITY REACTIONS INCLUDING ANAPHYLAXIS

Patients treated with enzyme replacement therapies have experienced life‑threatening hypersensitivity reactions, including anaphylaxis. Anaphylaxis has occurred during the early course of enzyme replacement therapy and after extended duration of therapy.

Initiate ELELYSO in a healthcare setting with appropriate medical monitoring and support measures, including access to cardiopulmonary resuscitation equipment. If a severe hypersensitivity reaction (e.g., anaphylaxis) occurs, discontinue ELELYSO and immediately initiate appropriate medical treatment, including use of epinephrine. Inform patients of the symptoms of life‑threatening hypersensitivity reactions, including anaphylaxis and to seek immediate medical care should symptoms occur [see Warnings and Precautions (5.1)].

1 INDICATIONS AND USAGE

ELELYSO is indicated for the treatment of patients 4 years of age and older with a confirmed diagnosis of Type 1 Gaucher disease.

2 DOSAGE AND ADMINISTRATION

2.1 Recommendations Prior to ELELYSO Treatment

Administration of ELELYSO should be supervised by a healthcare provider knowledgeable in the management of hypersensitivity reactions including anaphylaxis [see Warnings and Precautions (5.1)].

Initiate ELELYSO in a healthcare setting with appropriate medical monitoring and support measures, including access to cardiopulmonary resuscitation equipment [see Warnings and Precautions (5.1)].

To reduce the risk of hypersensitivity reactions, consider pretreatment with antihistamines and/or corticosteroids [see Warnings and Precautions (5.1)].

2.2 Recommended Dosage in Patients 4 Years and Older

Treatment-Naïve Patients 4 Years of Age and Older

The recommended dosage of ELELYSO is 60 units/kg (based on actual body weight) administered every other week as a 60- to 120-minute intravenous infusion.

Patients 4 Years of Age and Older Switching from Imiglucerase

If it is acceptable to switch from a stable imiglucerase dosage to ELELYSO, initiate ELELYSO intravenous treatment (60- to 120-minute infusion) with the same units/kg imiglucerase dosage and subsequently administer ELELYSO every other week. Dosage adjustments can be made based on achievement and maintenance of each patient's therapeutic goals.

2.3 Preparation Instructions

ELELYSO should be reconstituted, diluted, and administered under the supervision of a healthcare professional.

Prepare ELELYSO according to the following steps using aseptic technique:

a. Determine the number of vials to be reconstituted based on the patient's weight in kg and the recommended dose [see Dosage and Administration (2.2)]. Round the number of vials up to the next whole number.
b. Remove the required number of vials from the refrigerator. Do not leave these vials at room temperature longer than 24 hours prior to reconstitution. Do not heat or microwave these vials.
c. Reconstitute each vial of ELELYSO with 5.1 mL of Sterile Water for Injection, USP to yield a reconstituted product with a concentration of 40 units/mL and an extractable volume of 5 mL.
  (1) Upon reconstitution, mix vials gently. DO NOT SHAKE.
  (2) Prior to further dilution, visually inspect the reconstituted solution in the vials for particulate matter and discoloration. The solution should be clear and colorless. Discard if particulate matter is present or the solution is discolored.
d. Withdraw the calculated dose of drug from the appropriate number of vials and dilute with 0.9% Sodium Chloride Injection, USP, to a final volume of 100 to 200 mL. Discard any unused reconstituted solution.
  (1) For pediatric patients 4 years of age and older, use a final volume of 100 to 120 mL.
  (2) For adult patients, may use a final volume of 130 to 150 mL. However, if the volume of reconstituted product alone is equal to or greater than 130 to 150 mL, then the final volume should not exceed 200 mL.
e. Mix the diluted solution gently. DO NOT SHAKE. Since this is a protein solution, slight flocculation (described as translucent fibers) occurs occasionally after dilution.
f. Discard any unused diluted solution.

2.4 Storage and Handling of the Reconstituted and Diluted Solution

- If the reconstituted ELELYSO vial is not used immediately, refrigerate at 2 °C to 8 °C (36 °F to 46 °F) for up to 24 hours (under protection from light) or store at controlled room temperature at 20 °C to 25 °C (68 °F to 77 °F) for up to 4 hours (without protection from light).
- If the diluted solution is not administered immediately, refrigerate at 2 °C to 8 °C (36 °F to 46 °F) for up to 24 hours (under protection from light).
- The total storage time for the reconstituted and diluted solution should not exceed 24 hours. Discard the unused reconstituted or diluted solution after 24 hours from the start of preparation.
- Do not freeze.

2.5 Administration Instructions

After reconstitution and dilution, administer via intravenous infusion over a minimum of 60 minutes and with an in-line low protein-binding 0.2 micron filter.

- For pediatric patients who weigh (based on actual body weight):
  - Less than 30 kg use an infusion rate of 1 mL/minute.
  - Greater than or equal to 30 kg, use an initial infusion rate of 1 mL/minute. After tolerability to ELELYSO is established, may increase the infusion rate to a maximum of 2 mL/minute.
- For adult patients, use an initial infusion rate of 1.2 mL/minute. After tolerability to ELELYSO is established, may increase the infusion rate to a maximum of 2.2 mL/minute.

3 DOSAGE FORMS AND STRENGTHS

For injection: 200 units white to off-white lyophilized powder in a single-dose vial for reconstitution.

4 CONTRAINDICATIONS

None.

5 WARNINGS AND PRECAUTIONS

5.1 Hypersensitivity Reactions Including Anaphylaxis

Life‑threatening hypersensitivity reactions, including anaphylaxis, have occurred in patients treated with enzyme replacement therapies, including ELELYSO. In clinical trials, (patients were not routinely pretreated with antihistamines and/or corticosteroids prior to ELELYSO infusions during the clinical trials):

- 2 of 72 (3%) ELELYSO-treated patients experienced signs and symptoms consistent with anaphylaxis including urticaria, hypotension, flushing, wheezing, chest tightness, nausea, vomiting, and dizziness. These reactions occurred during ELELYSO infusion.
- 21 of 72 (29%) ELELYSO-treated patients experienced hypersensitivity reactions, including the 2 ELELYSO‑treated patients who experienced signs and symptoms consistent with anaphylaxis. Signs and symptoms of these hypersensitivity reactions included pruritus, angioedema, flushing, erythema, rash, nausea, vomiting, cough, chest tightness, and throat irritation. These reactions occurred during ELELYSO infusion and up to 3 hours after the start of infusion [see Adverse Reactions (6.1)].

Anaphylaxis has occurred during the early course of enzyme replacement therapy and after extended duration of therapy. Administration of ELELYSO should be supervised by a healthcare provider knowledgeable in the management of hypersensitivity reactions including anaphylaxis. Initiate ELELYSO in a healthcare setting with appropriate medical monitoring and support measures, including access to cardiopulmonary resuscitation equipment. Observe patients closely during and after the infusion.

ELELYSO-treated patients who developed anti-taliglucerase alfa antibodies (referred to as anti-drug antibodies (ADA)) generally had a greater frequency of hypersensitivity reactions compared to those who did not develop ADA [see Adverse Reactions (6.1)]. Closely monitor for hypersensitivity reactions in patients who develop ADA.

Management of hypersensitivity reactions should be based on the severity of the reaction and includes slowing or temporary interruption of the infusion and/or administration of antihistamines, antipyretics, and/or corticosteroids for mild reactions. To reduce the risk of hypersensitivity reactions, consider pretreatment with antihistamines and/or corticosteroids. If a severe hypersensitivity reaction (e.g., anaphylaxis) occurs, discontinue ELELYSO and immediately initiate appropriate medical treatment, including use of epinephrine.

Inform patients of the symptoms of life‑threatening hypersensitivity reactions, including anaphylaxis and to seek immediate medical care should symptoms occur.

Consider the risks and benefits of re-administering ELELYSO in patients who have experienced a severe hypersensitivity reaction associated with ELELYSO. Caution should be exercised upon rechallenge [see Adverse Reactions (6.2)].

6 ADVERSE REACTIONS

6.1 Clinical Trials Experience

Because clinical trials are conducted under widely varying conditions, adverse reaction rates observed in the clinical trials of a drug cannot be directly compared to rates in the clinical trials of another drug and may not reflect the rates observed in practice.

Adverse Reactions from Clinical Trials of ELELYSO as Initial Therapy

- Clinical Trial in Adult Patients
The safety of ELELYSO at dosages of either 30 units/kg (n=16) (50% of the recommended dosage) [see Dosage and Administration (2.1)] or 60 units/kg (n=16) administered intravenously every other week was assessed in 32 adult treatment-naïve patients (aged 19 to 74 years) with Type 1 Gaucher disease in a 9-month double-blind, randomized clinical trial (Trial 1) [see Clinical Studies (14)]. Table 1 presents the adverse reactions that occurred in these ELELYSO-treated patients.

Table 1: Adverse Reactions in ≥5% of Treatment-Naïve Adult Patients Treated with ELELYSO
Preferred Term | Treatment-Naïve Adults (N=32) n (%)
Headache | 6 (19)
Arthralgia | 4 (13)
Fatigue | 3 (9)
Nausea | 3 (9)
Dizziness | 3 (9)
Abdominal pain | 2 (6)
Pruritus | 2 (6)
Flushing | 2 (6)
Vomiting | 2 (6)
Urticaria | 2 (6)

- Clinical Trial in Pediatric Patients 16 Years of Age and Younger
The safety of ELELYSO at dosages of either 30 units/kg (n=4) (50% of the recommended dosage) [see Dosage and Administration (2.1)] or 60 units/kg (n=5) administered intravenously every other week was assessed in 9 pediatric treatment-naïve patients (aged 2 to 13 years) with Type 1 Gaucher disease in a 12-month randomized clinical trial (Trial 2) [see Clinical Studies (14)].

The most common adverse reaction (≥10%) was vomiting, which occurred in 4 of 9 patients. Two patients developed hypersensitivity reactions; 1 patient experienced severe vomiting and gastrointestinal inflammation, and 1 experienced mild throat irritation and chest discomfort. Both patients responded to treatment with antihistamines and continued ELELYSO treatment.

Adverse Reactions in a Clinical Trial in Patients Who Switched from Imiglucerase to ELELYSO

The safety of ELELYSO was assessed in 31 patients (26 adult and 5 pediatric patients), ages 6 to 66 years old, with Type 1 Gaucher disease who had previously been receiving imiglucerase treatment for a minimum of 2 years (Trial 3). ELELYSO was administered intravenously every other week for 9 months at the same number of units as each patient's previous imiglucerase dose. Table 2 presents the adverse reactions in these ELELYSO-treated patients.

Table 2: Adverse Reactions in ≥10% of ELELYSO-Treated Patients Who Switched from Imiglucerase to ELELYSO (after 9 months on treatment)
Preferred Term | Adult and Pediatric Patients Switched from Imiglucerase (N=31) n (%)
Arthralgia | 4 (13)
Headache | 4 (13)
Pain in extremity | 3 (10)

Immunogenicity: Anti-Drug Antibody-Associated Adverse Reactions

Trials 1, 2, and 3 evaluated ELELYSO enzyme replacement therapy (ERT)-naïve and ERT-experienced adult and pediatric patients with Gaucher disease [see Clinical Studies (14.1, 14.2)]. In patients with Type 1 Gaucher disease, hypersensitivity reactions occurred in 36% (9/25) of ELELYSO-treated patients who developed ADA during the treatment period and in 15% (6/41) of ELELYSO-treated patients who did not develop ADA during the treatment period [see Warnings and Precautions (5.1) and Clinical Pharmacology (12.6)]. Of the 9 ELELYSO-treated patients who tested positive for ADA and who developed hypersensitivity reactions, 2 patients had anaphylaxis and 1 additional patient discontinued ELELYSO due to hypersensitivity reactions.

6.2 Postmarketing Experience

The following adverse reactions have been identified during post-approval use of ELELYSO. Because these reactions include those reported voluntarily from a population of uncertain size in addition to those from postmarketing studies, it is not always possible to reliably estimate their frequency or establish a causal relationship to drug exposure:

- Gastrointestinal disorders: Vomiting, diarrhea
- General disorders and administration site conditions: Fatigue
- Immune system disorders: Anaphylaxis [see Warnings and Precautions (5.1)], Type III immune mediated fixed drug eruption
- Musculoskeletal and connective tissue disorders: Back pain

8 USE IN SPECIFIC POPULATIONS

8.1 Pregnancy

Risk Summary

Available data, including data from a product registry and pharmacovigilance reports, have not identified a drug-associated risk of major birth defects, miscarriage, or other adverse maternal or fetal outcomes in pregnant women exposed to ELELYSO. Additionally, there are risks associated with untreated symptomatic Type I Gaucher disease in pregnant women (see Clinical Considerations). In animal reproduction studies when pregnant rats and rabbits were administered taliglucerase alfa at intravenous doses up to 5 times the recommended human dose (RHD), there was no evidence of embryo-fetal toxicity (see Data).

The background risk of major birth defects and miscarriage for the indicated population is unknown. In the U.S. general population, the estimated background risk of major birth defects and miscarriage in clinically recognized pregnancies is 2 to 4% and 15 to 20%, respectively.

Clinical Considerations

Disease-Associated Maternal and/or Embryo/Fetal Risk

Women with Type 1 Gaucher disease have an increased risk of spontaneous abortion if disease symptoms are not treated and controlled pre-conception and during a pregnancy. Pregnancy may exacerbate existing Type 1 Gaucher disease symptoms or result in new disease manifestations. Type 1 Gaucher disease manifestations may lead to adverse pregnancy outcomes, including hepatosplenomegaly which can interfere with the normal growth of a fetus and thrombocytopenia which can lead to increased bleeding and possible postpartum hemorrhage requiring transfusion.

Data

Animal Data

Reproduction studies have been performed with taliglucerase alfa administered during the period of organogenesis in rats and rabbits. In rats, intravenous doses up to 55 mg/kg/day (about 5 times the RHD of 60 units/kg based on the body surface area) did not cause any adverse effects on embryo-fetal development. In rabbits, intravenous doses up to 27.8 mg/kg/day (about 5 times the RHD of 60 units/kg based on the body surface area) did not show any embryo-fetal toxicity.

8.2 Lactation

Risk Summary

There are no data on the presence of taliglucerase alfa in human milk or the effects of taliglucerase alfa on milk production. Lactation data from a product registry have not identified adverse reactions in infants exposed to taliglucerase alfa during breastfeeding. The developmental and health benefits of breastfeeding should be considered along with the mother’s clinical need for ELELYSO and any potential adverse effects on the breastfed child from ELELYSO or from the underlying maternal condition.

8.4 Pediatric Use

The safety and effectiveness of ELELYSO for the treatment of pediatric patients 4 years of age and older with a confirmed diagnosis of Type 1 Gaucher disease has been established. The use of ELELYSO for this indication is supported by evidence of effectiveness from adequate and well-controlled trials of ELELYSO in adults, with additional pharmacodynamic data from 5 pediatric patients and pharmacokinetic data from 9 pediatric patients who participated in clinical trials [see Clinical Studies (14.1, 14.2) and Clinical Pharmacology (12.3)]. Data from 14 pediatric patients were included in the safety evaluation [see Adverse Reactions (6.1)]. The safety and effectiveness of ELELYSO has not been established in patients less than 4 years of age.

Pediatric patients experienced a higher frequency of vomiting during ELELYSO treatment (4 of 9 treatment-naïve patients) than adult patients, and this may be a symptom of hypersensitivity reaction. The frequencies of other adverse reactions were similar between pediatric and adult patients treated with ELELYSO [see Adverse Reactions (6.1)].

8.5 Geriatric Use

During clinical trials, 8 patients aged 65 or older were treated with ELELYSO. Clinical trials of ELELYSO did not include sufficient numbers of patients aged 65 and over to determine whether they respond differently from younger patients.

11 DESCRIPTION

Taliglucerase alfa is a hydrolytic lysosomal glucocerebroside-specific enzyme produced by recombinant DNA technology using plant cell culture (carrot). Taliglucerase alfa is a monomeric glycoprotein enzyme containing 4 N-linked glycosylation sites (kDa=60.8). Taliglucerase alfa differs from native human glucocerebrosidase by 2 amino acids at the N terminal and up to 7 amino acids at the C terminal. Taliglucerase alfa is a glycosylated protein with oligosaccharide chains at the glycosylation sites having terminal mannose sugars. These mannose-terminated oligosaccharide chains of taliglucerase alfa are specifically recognized by endocytic carbohydrate receptors on macrophages, the cells that accumulate lipid in Gaucher disease.

A unit is the amount of enzyme that catalyzes the hydrolysis of 1 micromole of the synthetic substrate para-nitrophenyl-β-D-glucopyranoside (pNP-Glc) per minute at 37 °C.

ELELYSO (taliglucerase alfa) for injection is supplied as a sterile, preservative-free, lyophilized powder for reconstitution and dilution prior to intravenous infusion. Each single-dose vial contains 200 units of taliglucerase alfa and D-mannitol (206.7 mg), polysorbate 80 (0.56 mg), and sodium citrate (30.4 mg). Citric acid may be added to adjust the pH at the time of manufacture. After reconstitution with 5.1 mL Sterile Water for Injection, USP, taliglucerase alfa concentration is 40 units/mL [see Dosage and Administration (2)]. Reconstituted solutions have a pH of approximately 6.0.

12 CLINICAL PHARMACOLOGY

12.1 Mechanism of Action

Gaucher disease is an autosomal recessive disorder caused by mutations in the human glucocerebrosidase gene, which results in a reduced activity of the lysosomal enzyme glucocerebrosidase. Glucocerebrosidase catalyzes the conversion of the sphingolipid glucocerebroside into glucose and ceramide. The enzymatic deficiency results in accumulation of substrate glucocerebroside primarily in the lysosomal compartment of macrophages, giving rise to foam cells or "Gaucher cells," which accumulate in the liver, spleen and bone marrow.

ELELYSO, an enzyme replacement therapy, is a recombinant analog of human lysosomal glucocerebrosidase that catalyzes the hydrolysis of glucocerebroside to glucose and ceramide, reducing the amount of accumulated glucocerebroside. ELELYSO uptake into cellular lysosomes is mediated by binding of ELELYSO mannose oligosaccharide chains to specific mannose receptors on the cell surface leading to internalization and subsequent transport to the lysosomes.

12.3 Pharmacokinetics

Pharmacokinetics of taliglucerase alfa were evaluated in 38 patients (29 adult and 9 pediatric patients) who received intravenous infusions of ELELYSO 30 units/kg (50% of the recommended dosage) or 60 units/kg (the recommended dosage) [see Dosage and Administration (2.1)] every other week. The pharmacokinetic parameters in adult and pediatric patients are summarized in Table 3.

In adult Type 1 Gaucher disease patients treated with ELELYSO 30 units/kg (50% of the recommended dosage) or 60 units/kg (the recommended dosage) [see Dosage and Administration (2.1)] (N=29) every other week as initial therapy, pharmacokinetics were determined with the first dose and at Week 38 of treatment. The pharmacokinetics of taliglucerase alfa appeared to be nonlinear with a greater than dose-proportional increase in exposure at the doses studied.

No significant accumulation or change in taliglucerase alfa pharmacokinetics over time from Weeks 1 to 38 was observed with repeated dosages of 30 units/kg (50% of the recommended dosage) or 60 units/kg (the recommended dosage) [see Dosage and Administration (2.1)] every other week. Based on the limited data, there were no significant pharmacokinetic differences between male and female patients in this study.

The pharmacokinetics of taliglucerase alfa were evaluated in 9 pediatric patients 4 to 17 years of age with Type 1 Gaucher disease who were treated with ELELYSO for 10 to 27 months. Six of the 9 patients were treatment-naïve, and 3 patients were switched from imiglucerase. In both the 30 units/kg (50% of the recommended dosage) and 60 units/kg (the recommended dosage) [see Dosage and Administration (2.1)] dose groups, clearance values in pediatric patients were similar to those in adult patients. AUC values in pediatric patients were lower than AUC values in adult patients, due to weight-based dosing of taliglucerase alfa and lower body weights in pediatric patients.

Table 3: Taliglucerase Alfa Pharmacokinetic Parameters after Repeated Dosing in Adult and Pediatric Patients with Type 1 Gaucher Disease
 | Pediatric Patients (N=9) Median (Range) |  | Adult Patients at Week 38 (N=29) Median (Range)
 | 30 units/kg [30 units/kg is 50% of the recommended dose.] n=5 | 60 units/kg n=4 | 30 units/kg n=14 | 60 units/kg n=15
Age (years) | 15 (10, 17) | 11 (4, 16) | 35 (19, 74) | 33 (19, 58)
Weight (kg) | 44.3 (22.8, 71.0) | 28.6 (16.5, 50.4) | 72.5 (51.5, 99.5) | 73.5 (58.5, 87.0) [n=14]
AUC0–∞ (ng*h/mL) [Values were derived from concentration data expressed in ng/mL] | 1416 (535, 1969) | 2984 (1606, 4273) | 2007 (1007, 10092) | 6459 (2548, 21020)
T1/2 (min) | 37.1 (22.5, 56.8) | 32.5 (18.0, 42.9) | 18.9 (9.20, 57.9) | 28.7 (11.3, 104)
CL (L/h) | 30.5 (17.4, 37.8) | 15.8 (11.7, 24.9) | 30.5 (6.79, 68.0) | 18.5 (6.20, 37.9)
Vss (L) | 14.9 (10.1, 35.6) | 8.80 (3.75, 21.4) | 11.7 (2.3, 22.7) | 10.7 (1.4, 18.5)

12.6 Immunogenicity

The observed incidence of ADA (including neutralizing antibodies [Nab]) is highly dependent on the sensitivity and specificity of the assay. Differences in assay methods preclude meaningful comparisons of the incidence of ADA in the studies described below with the incidence of ADA in other studies, including those of ELELYSO or of other taliglucerase alfa products.

Anti-Drug Antibodies

In Trials 1, 2, and 3, a greater portion of ELELYSO-treated patients who developed ADA had hypersensitivity reactions compared to those who did not develop ADA [see Adverse Reactions (6.1) and Warnings and Precautions (5.1)].

In Trial 1 (treatment-naïve adults with Gaucher disease) [see Clinical Studies (14.1)], 17 (53%) of 32 ELELYSO-treated patients developed ADA. Additionally 2 (6%) patients tested positive for ADA at baseline prior to ELELYSO treatment.

In Trial 2 (treatment-naïve pediatric patients with Gaucher disease) [see Clinical Studies (14.1)], 2 (22%) of 9 Type 1 Gaucher disease ELELYSO-treated patients developed ADA. Additionally, 1 patient was ADA-positive prior to initiation of ELELYSO.

In Trial 3 (switched from imiglucerase to ELELYSO), of 31 ELELYSO-treated patients (26 adult and 5 pediatric patients) [see Clinical Studies (14.2)], 6 adults (23% of adult patients) developed ADA and no pediatric patient developed ADA. Additionally, 3 (10%) patients were ADA positive prior to initiation of ELELYSO.

There is insufficient information to characterize the ADA response to ELELYSO and the effects of ADA on pharmacokinetics, pharmacodynamics, or effectiveness of taliglucerase alfa products.

Neutralizing Antibodies

In Trials 1, 2 and 3 with a total number of 72 patients, 30 of the 31 ELELYSO-treated adult and pediatric patients who developed ADA or tested positive for ADA at baseline were evaluated for neutralizing activity of the ADA in the mannose receptor binding and enzyme activity assays.

- Nineteen (63%) of the 30 patients had neutralizing antibodies (Nab) capable of inhibiting in vitro mannose receptor binding of ELELYSO.
- Eight (42%) of these 19 patients had Nab capable of inhibiting the in vitro enzymatic activity of ELELYSO.

Although the effectiveness was numerically lower (less spleen and liver volume reduction) in ELELYSO-treated patients who developed Nab compared to those that did not develop Nab, the data were not sufficient to fully assess whether the observed Nab reduces effectiveness.

Other Antibodies

Nine (29%) of the 31 ELELYSO-treated adult and pediatric patients who developed ADA during treatment or tested positive for ADA at baseline also developed antibodies against plant-specific glycans in ELELYSO.

13 NONCLINICAL TOXICOLOGY

13.1 Carcinogenesis, Mutagenesis, Impairment of Fertility

Long-term studies in animals to evaluate carcinogenic potential or studies to evaluate mutagenic potential have not been performed with taliglucerase alfa. In a male and female fertility study in rats, taliglucerase alfa did not cause any significant adverse effect on male or female fertility parameters up to a maximum dose of 55 mg/kg/day (about 5 times the recommended human dose of 60 units/kg based on the body surface area).

14 CLINICAL STUDIES

14.1 Clinical Trials of ELELYSO as Initial Therapy

Clinical Trial in Adult Patients

The safety and efficacy of ELELYSO in the treatment of adult patients with Type 1 Gaucher disease was assessed in a 9-month, multi-center, double-blind, randomized trial (Trial 1) in 31 adult patients with Gaucher disease-related enlarged spleens (>8 times normal) and thrombocytopenia (<120,000 /mm^3). Sixteen patients had enlarged livers and 10 patients had anemia at baseline. All patients were naïve to enzyme replacement therapy (ERT). Patients with severe neurological symptoms were excluded from the trial.

Patients were randomized to receive ELELYSO at an intravenous dosage of either 30 units/kg (n=15) (50% of the recommended dosage) or 60 units/kg (the recommended dosage) [see Dosage and Administration (2.1)] (n=16) every other week. After 9 months, 26 of the 31 patients continued in the blinded portion of the long-term extension trial for a total treatment duration of 24 months at the same intravenous dosage every other week. Twenty-three of those 26 patients continued open-label ELELYSO treatment (30 or 60 units/kg given intravenously every other week) for an additional 12 months (total duration of ELELYSO treatment was 36 months).

Baseline Demographics

In Trial 1, patients were 19 to 74 years of age (mean age 36 years), 48% were male, 97% were White and 29% and 71% were Hispanic/Latino and non Hispanic/Latino, respectively.

Efficacy Results

Table 4 shows the baseline values and mean (SD) changes in clinical parameters (spleen volume, liver volume, platelet count, and hemoglobin) after 9 months of ELELYSO treatment in Trial 1. Liver and spleen volumes were measured by MRI and are reported as percentage of body weight (%BW) and multiples of normal (MN). The observed reduction from baseline in spleen volume (the primary endpoint), was considered to be clinically meaningful in light of the natural history of untreated Gaucher disease.

Table 4: Mean (SD [SD = standard deviation]) Changes in Clinical Parameters from Baseline to 9 Months in Treatment-Naïve Adults with Type 1 Gaucher Disease Treated with ELELYSO (N=31) (Trial 1)
 | Clinical Parameter | ELELYSO; 30 units/kg [The recommended ELELYSO dosage in treatment-naïve adult patients is 60 units/kg every other week. ELELYSO 30 units/kg every other week is not a recommended dosage. [see Dosage and Administration (2.1)]] (n=15) Mean (SD) | ELELYSO; 60 units/kg (n=16) Mean (SD)
Spleen Volume (%BW [%BW = percentage of body weight]) | Baseline | 3.1 (1.5) | 3.3 (2.7)
Spleen Volume (%BW [%BW = percentage of body weight]) | Month 9 | 2.2 (1.3) | 2.1 (1.9)
Spleen Volume (%BW [%BW = percentage of body weight]) | Change | -0.9 (0.4) | -1.3 (1.1)
Spleen Volume (MN [MN = multiples of normal]) | Baseline | 15.4 (7.7) | 16.7 (13.4)
Spleen Volume (MN [MN = multiples of normal]) | Month 9 | 11.1 (6.3) | 10.4 (9.4)
Spleen Volume (MN [MN = multiples of normal]) | Change | -4.5 (2.1) | -6.6 (5.4)
Liver Volume (%BW) | Baseline | 4.2 (0.9) | 3.8 (1.0)
Liver Volume (%BW) | Month 9 | 3.6 (0.7) | 3.1 (0.7)
Liver Volume (%BW) | Change | -0.6 (0.5) | -0.6 (0.4)
Liver Volume (MN) | Baseline | 1.7 (0.4) | 1.5 (0.4)
Liver Volume (MN) | Month 9 | 1.4 (0.3) | 1.2 (0.3)
Liver Volume (MN) | Change | -0.2 (0.2) | -0.3 (0.2)
Platelet Count (mm^3) | Baseline | 75,320 (40,861) | 65,038 (28,668)
Platelet Count (mm^3) | Month 9 | 86,747 (50,989) | 106,531 (53,212)
Platelet Count (mm^3) | Change | 11,427 (20,214) | 41,494 (47,063)
Hemoglobin (g/dl) | Baseline | 12.2 (1.7) | 11.4 (2.6)
Hemoglobin (g/dl) | Month 9 | 14.0 (1.4) | 13.6 (2.0)
Hemoglobin (g/dl) | Change | 1.6 (1.4) | 2.2 (1.4)

The following data are the changes in clinical parameters from baseline to Month 24 (including the 9-month initial period and the 15-month first long-term extension) for the 30 units/kg (n=12) (50% of the recommended dosage) and 60 units/kg (the recommended dosage) [see Dosage and Administration (2.1)] (n=14) treatment groups, respectively: mean (SD) spleen volume (%BW) decreased by 1.4 (0.6) and 2.0 (2.0), in MN by 6.8 (3.0) and 10.2 (9.8); hemoglobin increased by 1.3 (1.7) g/dL and 2.4 (2.3) g/dL; liver volume (%BW) decreased by 1.1 (0.5) and 1.0 (0.7), in MN by 0.4 (0.2) and 0.4 (0.3 and platelet count increased 28,433 (31,996)/mm^3 and 72,029 (68,157)/mm^3. The 23 patients who continued open-label ELELYSO treatment for additional 12 months demonstrated stability in these clinical parameters.

Clinical Trial in Pediatric Patients 16 Years of Age and Younger

The safety and efficacy of ELELYSO in the treatment of pediatric patients with Type 1 Gaucher disease was assessed in a 12-month, multi-center, double-blind, randomized trial (Trial 2) in 9 treatment-naïve patients. Patients were randomized to receive ELELYSO at an intravenous dosage of either 30 units/kg (n=4) (50% of the recommended dosage) or 60 units/kg (the recommended dosage) [see Dosage and Administration (2.1)] (n=5) every other week. After 12 months, all 9 patients entered a blinded portion of the long-term extension trial (24 months of total treatment) where they continued treatment with ELELYSO at the same dosage every other week.

Baseline Demographics

In Trial 2, patients were 2 to 13 years of age (mean age 8.1 years), 67% were male, 89% were White and 44% and 56% were Hispanic/Latino and non Hispanic/Latino, respectively.

Efficacy Results

The following data in Trial 2 are the changes [median (Q1, Q3)] in clinical parameters from baseline to Month 12 for the 60 units/kg dose group (n=5): spleen volume decreased from 18.4 (14.2, 35.1) MN to 11.0 (8.3, 14.5) MN; hemoglobin increased from 11.1 (9.2, 11.3) g/dL to 11.7 (11.5, 12.9) g/dL; liver volume decreased from 2.1 (2.0, 2.3) MN to 1.6 (1.5, 1.9) MN; platelet count increased from 80,000 (79,000, 87,000)/mm^3 to 131,000 (119,000, 215,000)/mm^3.

The following data are the changes [median (Q1, Q3)] in clinical parameters from baseline to Month 24 (including the initial 12-month period and the 12-month long-term extension) for the 60 units/kg dose group (n=5): spleen volume decreased by 19.0 (8.3, 41.2) MN; hemoglobin increased by 2.5 (1.9, 3.0) g/dL; liver volume decreased by 0.8 (0.6, 1.1) MN; and platelet count increased by 76,000 (67,000, 100,000)/mm^3.

14.2 Clinical Trial in Patients Switching from Imiglucerase Treatment to ELELYSO

The safety and efficacy of ELELYSO were assessed in 31 patients (26 adult and 5 pediatric patients) with Type 1 Gaucher disease who were switched from imiglucerase to ELELYSO (Trial 3). Trial 3 was a 9-month, multi-center, open-label, single arm study in patients who had been receiving intravenous treatment with imiglucerase at dosages ranging from 9.5 units/kg to 60 units/kg every other week for a minimum of 2 years. Patients were required to be clinically stable and have a stable biweekly dosage of imiglucerase for at least 6 months prior to enrollment. Imiglucerase therapy was stopped, and treatment with ELELYSO was administered every other week at the same number of units as each patient's previous imiglucerase dose (9.5 units/kg to 60 units/kg given intravenously every other week). If needed, adjustment of dosage was allowed during the study in order to maintain stability of clinical parameters (i.e., spleen volume, liver volume, platelet count, and hemoglobin).

- Eighteen of the 26 adult patients who completed the 9-month clinical trial continued treatment with ELELYSO (9.5 units/kg to 60 units/kg given intravenously every other week) in an open-label extension trial for additional 27 months (total duration of ELELYSO treatment was 36 months).
- Five of the pediatric patients who completed the 9-month trial continued open-label treatment with ELELYSO (9.5 units/kg to 60 units/kg given intravenously every other week) for additional 24 months (total duration of ELELYSO treatment was 33 months).

Baseline Demographics

In Trial 3, patients were 6 to 66 years of age (mean age 42 years, including pediatric patients), 55% were male, 97% were White, and 16% and 84% were Hispanic/Latino and non Hispanic/Latino, respectively.

Efficacy Results

In Trial 3, at baseline, spleen volume was 5.2 (4.5) MN, liver volume was 1.0 (0.3) MN, platelet count was 161,137 (73,387)/mm^3, and hemoglobin was 13.5 (1.4) g/dL. Mean (SD) organ volumes and hematologic values remained stable through 9 months of ELELYSO treatment. After 9 months of ELELYSO treatment, spleen volume was 4.8 (4.6) MN, liver volume was 1.0 (0.2) MN, platelet count was 161,167 (80,820)/mm^3, and hemoglobin was 13.4 (1.5) g/dL. The ELELYSO dosage remained unchanged in 30 of 31 patients. One patient required a dose increase at Week 24 (from 9.5 units/kg to 19 units/kg) for a platelet count of 92,000/mm^3 at Week 22, which subsequently increased to 170,000/mm^3 at Month 9.

During the 36‑month period, 18 ELELYSO-treated adult patients maintained stability in clinical parameters (spleen volume, liver volume, platelet count and hemoglobin); however only 10 of 18 adult patients completed 27 months of ELELYSO treatment in the extension trial and only 7 patients had their spleen and liver volumes assessed at 36 months.

During the 33-month period, the 5 ELELYSO-treated pediatric patients demonstrated stability in these clinical parameters.

16 HOW SUPPLIED/STORAGE AND HANDLING

ELELYSO (taliglucerase alfa) for injection is supplied as a sterile, preservative-free, white to off-white lyophilized powder in a single-dose vial. Each vial of ELELYSO contains 200 units of taliglucerase alfa.

Each carton contains one vial (NDC 0069-0106-01).

STORAGE AND HANDLING

Refrigerate ELELYSO at 2 °C to 8 °C (36 °F to 46 °F) in the original carton to protect from light. Do not freeze.

17 PATIENT COUNSELING INFORMATION

Hypersensitivity Reactions Including Anaphylaxis

Advise patients and caregivers that life-threatening hypersensitivity reactions, including anaphylaxis may occur with ELELYSO treatment.

Advise patients and caregivers that anaphylaxis has occurred during the early course of enzyme replacement therapy and after extended duration of therapy.

Inform patients and caregivers of the symptoms of life‑threatening hypersensitivity reactions, including anaphylaxis and to seek immediate medical care should symptoms occur [see Warnings and Precautions (5.1)].

This product’s labeling may have been updated. For the most recent prescribing information, please visit www.pfizer.com.

Manufactured by
Pfizer Inc.
NY, NY 10001
US License No. 2001

LAB-0610-17.0

PRINCIPAL DISPLAY PANEL - 200 unit Vial Label

NDC 0069-0106-01

Pfizer

Elelyso®
(taliglucerase alfa)
for injection

200 units/vial

For intravenous infusion only

Single-Dose Vial. Discard
any unused portion.
Rx only

PRINCIPAL DISPLAY PANEL - 200 unit Vial Carton

NDC 0069-0106-01

Pfizer

Elelyso®
(taliglucerase alfa)
for injection

200 units/vial

For intravenous infusion only

ANTI- COUNTERFEIT
LABEL PLACEMENT
NO VARNISH
NO COPY
NO INK

Single-Dose Vial. Discard any
unused portion.
Rx only